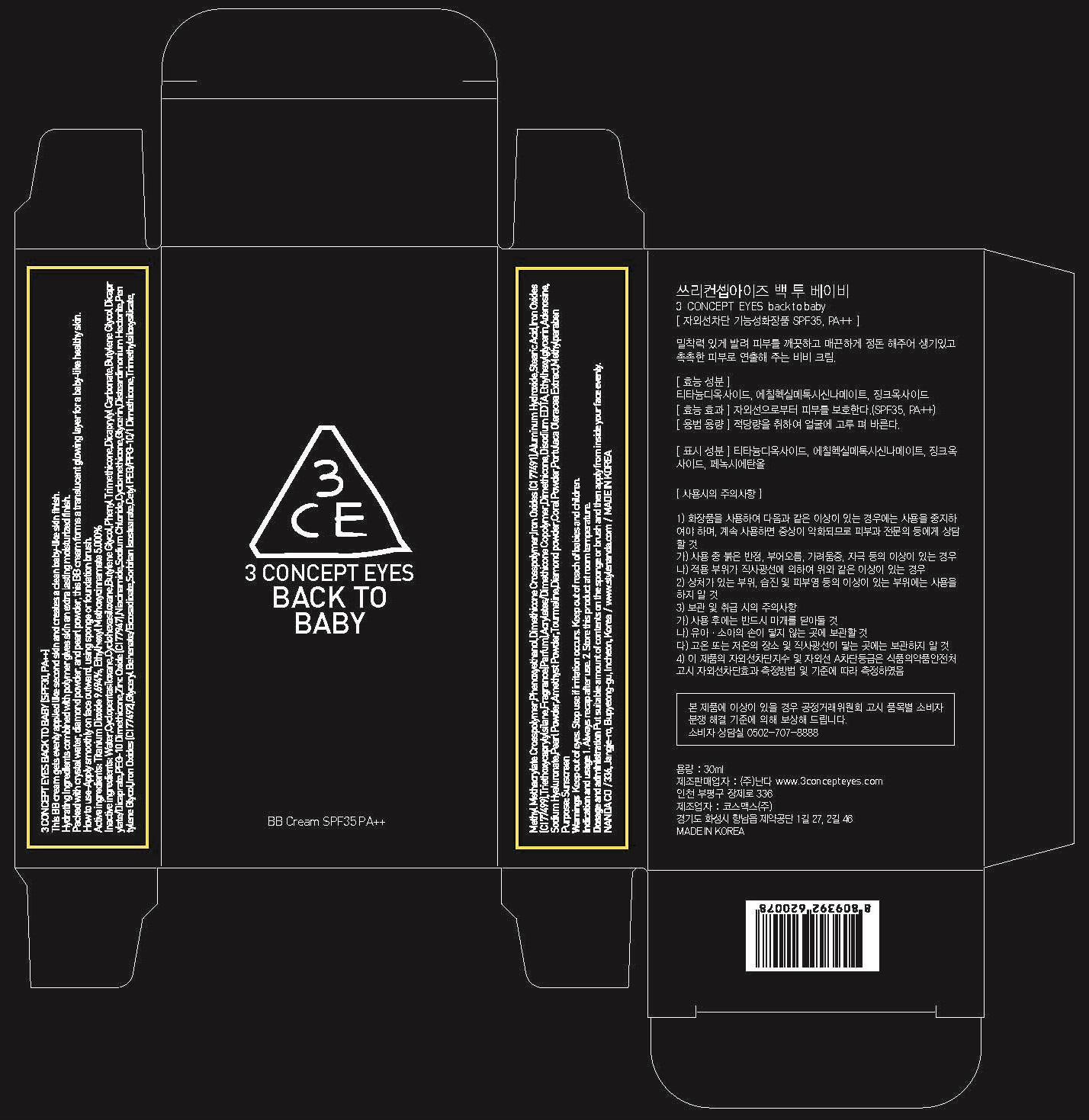 DRUG LABEL: 3 CONCEPT EYES BACK TO BABY
NDC: 60764-011 | Form: CREAM
Manufacturer: NANDA CO., LTD.
Category: otc | Type: HUMAN OTC DRUG LABEL
Date: 20140205

ACTIVE INGREDIENTS: Titanium Dioxide 2.90 mg/30 mL; OCTINOXATE 1.5 mg/30 mL
INACTIVE INGREDIENTS: Water; Butylene Glycol

ACTIVE INGREDIENT

Active ingredients: Titanium Dioxide 9.694%, Ethylhexyl Methoxycinnamate 5.000%

INACTIVE INGREDIENT

Inactive ingredients: Water,Cyclopentasiloxane, Butylene Glycol, Phenyl Trimethicone, Dicaprylyl Carbonate, Butylene Glycol Dicaprylate/Dicaprate, PEG-10 Dimethicone, Zinc Oxide (CI 77947), Niacinamide, Sodium Chloride, Cyclomethicone, Glycerin, Disteardimonium Hectorite, Pentylene Glycol, Iron Oxides (CI 77492), Glyceryl Behenate/Eicosadioate, Sorbitan Isostearate, Cetyl PEG/PPG-10/1 Dimethicone, Trimethylsiloxysilicate, Methyl Methacrylate Crosspolymer, Phenoxyethanol, Dimethicone Crosspolymer, Iron Oxides (CI 77491), Aluminum Hydroxide, Stearic Acid, Iron Oxides (CI 77499), Triethoxycaprylylsilane, Fragrance(Parfum), Acrylates/Dimethicone Copolymer, Dimethicone, Disodium EDTA,Ethylhexylglycerin, Adenosine, Sodium Hyaluronate, Pearl Powder, Amethyst Powder, Tourmaline, Diamond powder, Coral Powder, Portulaca Oleracea Extract, Methylparaben

PURPOSE

Purpose: Sunscreen

WARNINGS

Keep out of eyes.
Stop use if irritation occurs.
Keep out of reach of babies and children.

KEEP OUT OF REACH OF CHILDREN

Keep out of reach of babies and children.

INDICATIONS AND USAGE

Indication and usage:
1. Always recap after use.
2. Store this product at room temperature.

DOSAGE AND ADMINISTRATION

Put suitable amount of contents on the sponge or brush and then apply from inside your face evenly.